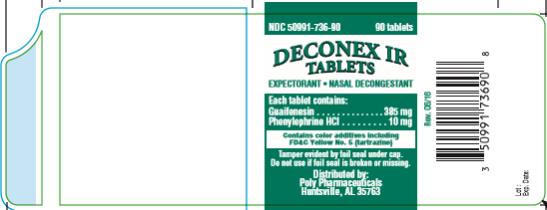 DRUG LABEL: Deconex IR
NDC: 50991-736 | Form: TABLET
Manufacturer: Poly Pharmaceuticals, Inc.
Category: otc | Type: HUMAN OTC DRUG LABEL
Date: 20240709

ACTIVE INGREDIENTS: GUAIFENESIN 385 mg/1 1; PHENYLEPHRINE HYDROCHLORIDE 10 mg/1 1
INACTIVE INGREDIENTS: FD&C YELLOW NO. 5; FD&C BLUE NO. 1; MAGNESIUM STEARATE; CELLULOSE, MICROCRYSTALLINE; SODIUM STARCH GLYCOLATE TYPE A POTATO

Deconex IR Tablets

Deconex IR

Drug Facts

Active ingredients

Guaifenesin 385 mg

Purpose

Expectorant

Active ingredients

Phenylephrine HCl 10 mg

Purpose

Nasal Decongestant

Uses

Temporarily relieves these symptoms due to the common cold, hay fever (allergic rhinitis) or other respiratory allergies:

- helps loosen phlegm and thin bronchial secretions to make coughs more productive
- nasal congestion
- runny nose
- sneezing
- itching of the nose or throat
- itchy, watery eyes

Warnings

Do not exceed recommended dosage.

A persistent cough may be a sign of a serious condition. If cough persists for more than 1 week, tends to recur, or is accompanied by fever, rash, or persistent headache, consult a doctor.

Ask a doctor before use if you have

- a persistent or chronic cough such as occurs with smoking, asthma, chronic bronchitis, or emphysema, or if cough is accompanied by excessive phlegm
- heart disease
- high blood pressure
- thyroid disease
- diabetes
- difficulty in urination due to enlargement of the prostate gland

Ask a doctor before use if you are taking sedatives or tranquilizers.

Stop use and ask a doctor if

- nervousness, dizziness or sleeplessness occur

Ask a doctor or pharmacist before use

if you are now taking a prescription monoamine oxidase inhibitor (MAOI) (certain drugs for depression, psychiatric, or emotional conditions, or Parkinson’s disease), or for 2 weeks after stopping the MAOI drug. If you do not know if your prescription drug contains an MAOI, ask a doctor or pharmacist before taking this product.

If pregnant or breast feeding,

ask a health professional before use.

Keep out of reach of children.

In case of overdose, get medical help or contact a Poison Control Center right away.

Directions:

Adults and children 12 years of age and older: 1 tablet every 4 hours, not to exceed 6 tablets in 24 hours.

Children age 6 to 12 years of age: 1/2 tablet every 4 hours, not to exceed 3 tablets in 24 hours or as directed by a doctor.

Children 6 years of age and younger: Consult a physician.

Other information

Tamper evident: do not use if tamper evident seal is broken or missing. Store at 15°-30°C (59°-86°F).

Deconex IR Tablets are a green, oval, scored tablet debossed POLY 716 on one side, plain on the other.

Inactive ingredients

FD&C Yellow No. 5, FD&C Blue No. 1, magnesium stearate, microcrystalline cellulose, sodium starch glycolate.

Manufactured for:
Poly Pharmaceuticals
Huntsville, AL 35763
(800) 882-1041
Rev. 06/16

PRINCIPAL DISPLAY PANEL

NDC 50991-736-90
Deconex IR
Tablets
90 Tablets